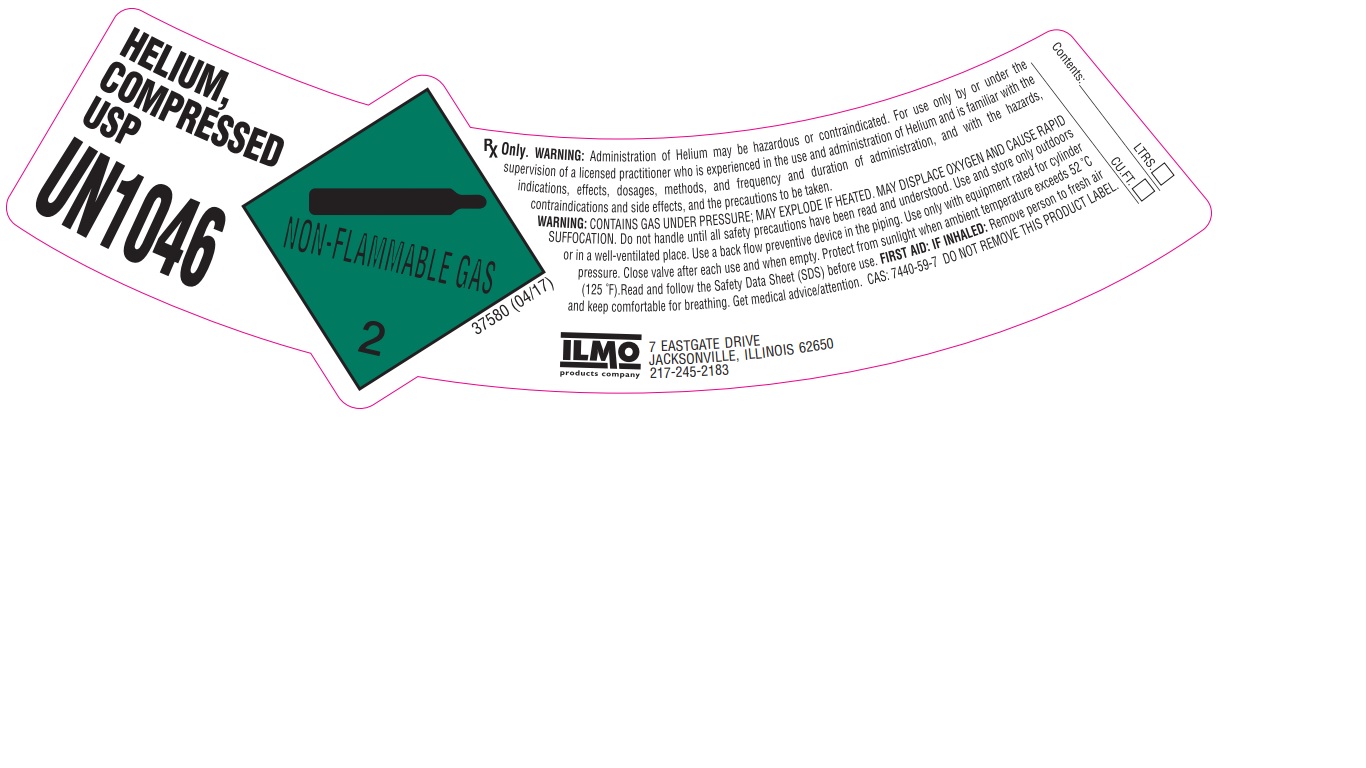 DRUG LABEL: Helium
NDC: 51486-020 | Form: GAS
Manufacturer: ILMO Products Company
Category: prescription | Type: HUMAN PRESCRIPTION DRUG LABEL
Date: 20251029

ACTIVE INGREDIENTS: HELIUM 990 mL/1 L

Helium

PACKAGE LABEL

HELIUM, COMPRESSED USP

UN1046

RX Only. WARNING: Administration of Helium may be hazardous or contraindicated. For use only by or under the supervision of a licensed practitioner who is experienced in the use and administration of Helium and is familiar with the indications, effects, dosages, methods, and frequency and duration of administration, and with the hazards, contraindications and side effects, and the precautions to be taken.

WARNING: CONTAINS GAS UNDER PRESSURE; MAY EXPLODE IF HEATED. MAY DISPLACE OXYGEN AND CAUSE RAPID SUFFOCATION. Do not handle until all safety precautions have been read and understood. Use and store only outdoors or in a well-ventilated place. Use a back flow preventive device in the piping. Use only with equipment rated for cylinder pressure. Close valve after each use and when empty. Protect from sunlight when ambient temperature exceeds 52 C (125 F). Read and follow the Safety Data Sheet (SDS) before use. FIRST AID: IF INHALED: Remove person to fresh air and keep comfortable for breathing. Get medical advice/attention. CAS: 7440-59-7 DO NOT REMOVE THIS PRODUCT LABEL.

ILMO products company

7 EASTGATE DRIVE

JACKSONVILLE, ILLINOIS 62650

217-245-2183